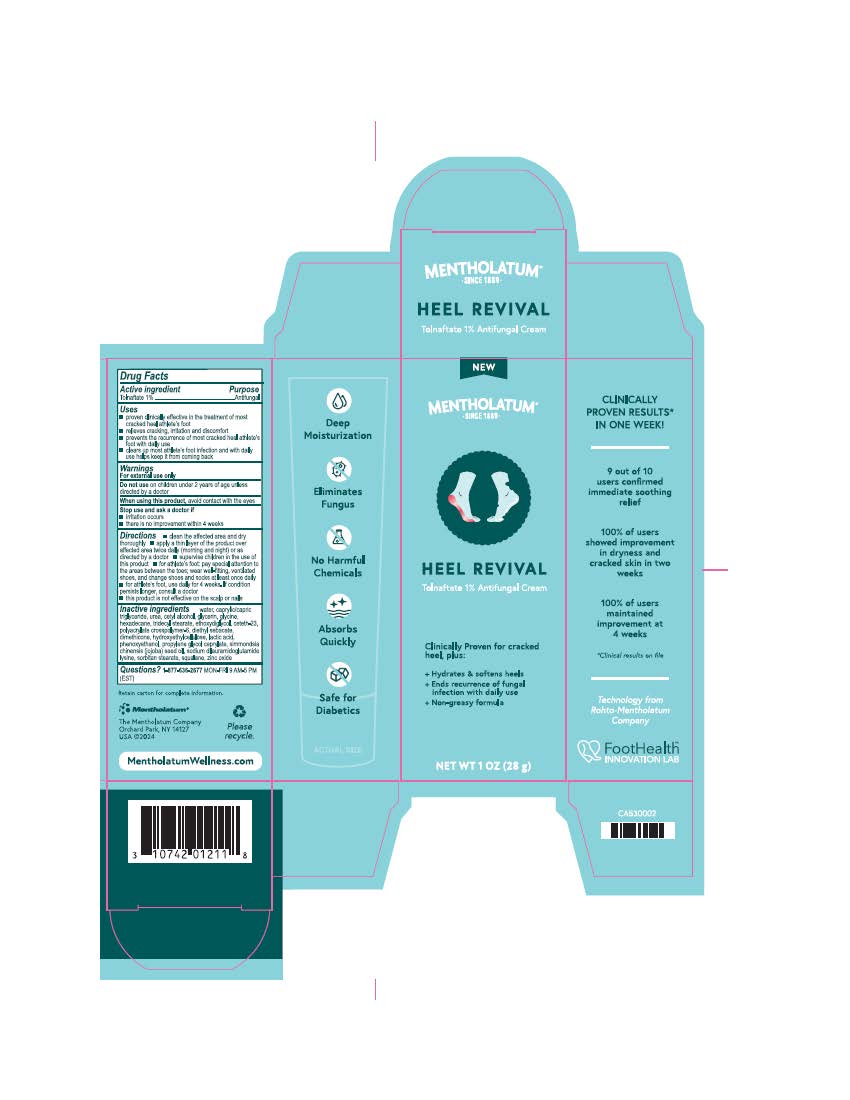 DRUG LABEL: Mentholatum Heel Revival Cream
NDC: 10742-0020 | Form: CREAM
Manufacturer: The Mentholatum Company
Category: otc | Type: HUMAN OTC DRUG LABEL
Date: 20240909

ACTIVE INGREDIENTS: TOLNAFTATE 10 mg/1 g
INACTIVE INGREDIENTS: ZINC OXIDE; GLYCERIN; ETHOXYDIGLYCOL; DIPROPYLENE GLYCOL CAPRYLATE; CETETH-23; SIMMONDSIA CHINENSIS (JOJOBA) SEED OIL; WATER; CAPRYLIC/CAPRIC TRIGLYCERIDE; DIETHYL SEBACATE; SORBITAN STEARATE; PHENOXYETHANOL; HEXADECANE; POLYACRYLATE CROSSPOLYMER-6; CETYL ALCOHOL; LACTIC ACID; DIMETHICONE; UREA; HYDROXYETHYLCELLULOSE; SQUALANE; GLYCINE; SODIUM DILAURAMIDOGLUTAMIDE LYSINE; TRIDECYL STEARATE

Drug Facts

Active ingredient

Tolnaftate 1%

Purpose

Tolnaftate - Antifungal

Uses

- proven clinically effective in the treatment of most cracked heel athlete’s foot
- relieves cracking, irritation and discomfort
- prevents the recurrence of most cracked heel athlete's foot with daily use
- Clears up most athlete’s foot infection and with daily use helps keep it from coming back

Warnings

For external use only

Do not use

on children under 2 years of age unless directed by a doctor.

When using this product,

avoid contact with the eyes.

Stop use and ask a doctor if

- irritation occurs
- there is no improvement within 4 weeks

Directions

- clean the affected area and dry thoroughly
- apply a thin layer of the product over affected area twice daily (morning and night) or as directed by a doctor
- supervise children in the use of this product
- for athlete’s foot: pay special attention to the areas between the toes; wear well-fitting, ventilated shoes, and change shoes and socks at least once daily
- for athlete's foot, use daily for 4 weeks. If condition persists longer, consult a doctor
- this product is not effective on the scalp or nails

Inactive ingredients

water, caprylic/capric triglyceride, urea, cetyl alcohol, glycerin, glycine, hexadecane, tridecyl stearate, ethoxydiglycol, ceteth-23, polyacrylate crosspolymer-6, diethyl sebacate, dimethicone, hydroxyethylcellulose, lactic acid, phenoxyethanol, propylene glycol caprylate, simmondsia chinensis (jojoba) seed oil, sodium dilauramidoglutamide lysine, sorbitan stearate, squalane, zinc oxide

Questions?

1-877-636-2677 MON-FRI 9AM-5PM (EST)

Keep Out of Reach of Children

If swallowed, get medical help or contact a Poison Control Central right away

Drug Facts

Prinicipal Display Panel